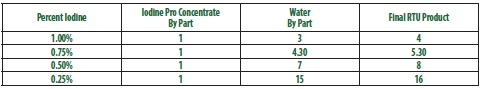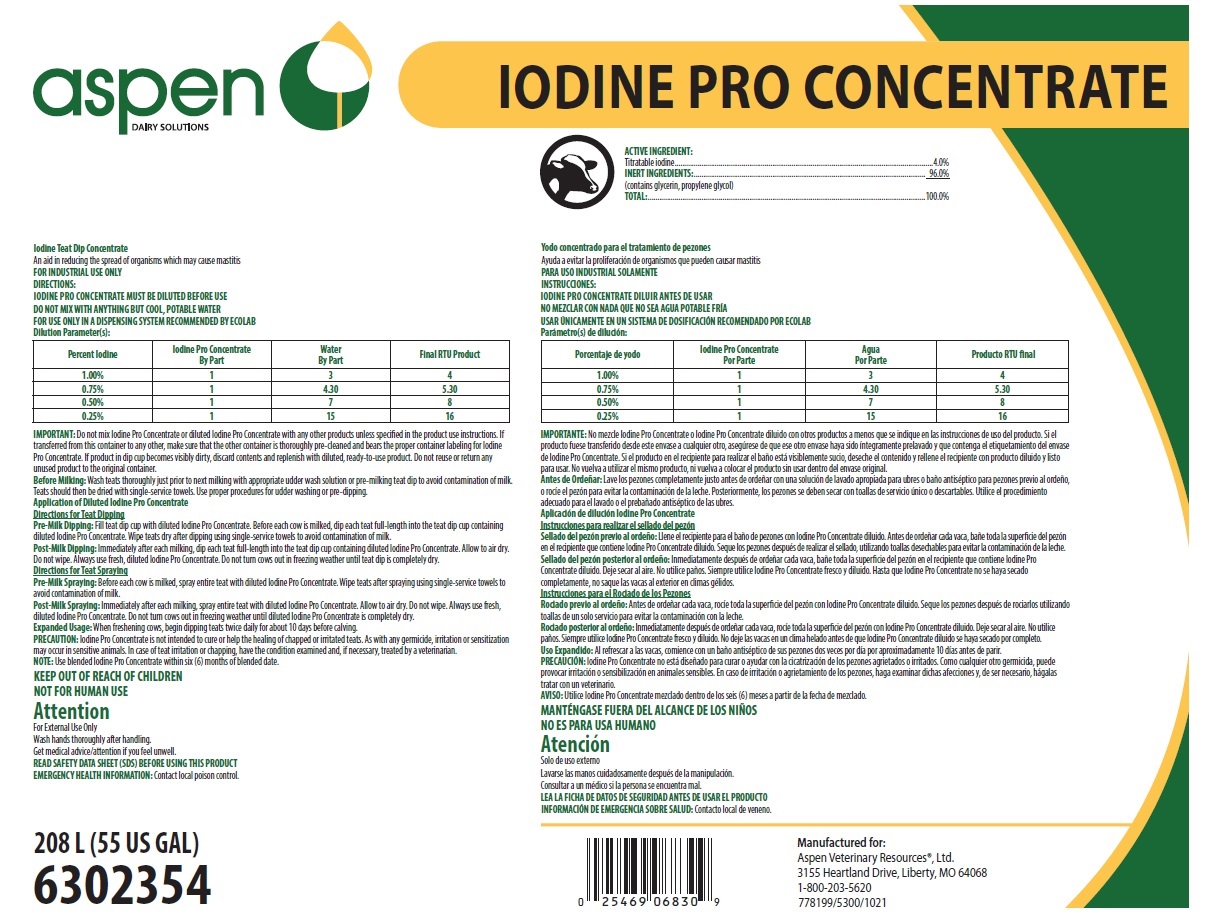 DRUG LABEL: Iodine Pro Concentrate
NDC: 46066-427 | Form: SOLUTION, CONCENTRATE
Manufacturer: Aspen Veterinary
Category: animal | Type: OTC ANIMAL DRUG LABEL
Date: 20250311

ACTIVE INGREDIENTS: IODINE 40 mg/1 mL
INACTIVE INGREDIENTS: WATER; GLYCERIN; PROPYLENE GLYCOL

KEEP OUT OF REACH OF CHILDREN

NOT FOR HUMAN USE

Attention

For External Use Only

Wash hands thoroughly after handling.

Get medical advice/attention if you feel unwell.

FOR INDUSTRIAL USE ONLY

OTHER SAFETY INFORMATION

READ SAFETY DATA SHEET (SDS) BEFORE USING THIS PRODUCT

EMERGENCY HEALTH INFORMATION: Contact local poison control.

DIRECTIONS:

IODINE PRO CONCENTRATE MUST BE DILUTED BEFORE USE

DO NOT MIX WITH ANYTHING BUT COOL, POTABLE WATER

FOR USE ONLY IN A DISPENSING SYSTEM RECOMMENDED BY ECOLAB

Dilution Parameter(s):

IMPORTANT: Do not mix Iodine Pro Concentrate or diluted Iodine Pro Concentrate with any other products unless specified in the product use instructions. If transferred from this container to any other, make sure that the other container is thoroughly pre-cleaned and bears the proper container labeling for Iodine Pro Concentrate. If product in dip cup becomes visibly dirty, discard contents and replenish with diluted, ready-to-use product. Do not reuse or return any unused product to the original container.

Before Milking: Wash teats thoroughly just prior to next milking with appropriate udder wash solution or pre-milking teat dip to avoid contamination of milk. Teats should then be dried with single-service towels. Use proper procedures for udder washing or pre-dipping.

Application of Diluted Iodine Pro Concentrate

Directions for Teat Dipping

Pre-Milk Dipping: Fill teat dip cup with diluted Iodine Pro Concentrate. Before each cow is milked, dip each teat full-length into the teat dip cup containing diluted Iodine Pro Concentrate. Wipe teats dry after dipping using single-service towels to avoid contamination of milk.

Post-Milk Dipping: Immediately after each milking, dip each teat full-length into the teat dip cup containing diluted Iodine Pro Concentrate. Allow to air dry. Do not wipe. Always use fresh, diluted Iodine Pro Concentrate. Do not turn cows out in freezing weather until teat dip is completely dry.

Directions for Teat Spraying

Pre-Milk Spraying: Before each cow is milked, spray entire teat with diluted Iodine Pro Concentrate. Wipe teats after spraying using single-service towels to avoid contamination of milk.

Post-Milk Spraying: Immediately after each milking, spray entire teat with diluted Iodine Pro Concentrate. Allow to air dry. Do not wipe. Always use fresh, diluted Iodine Pro Concentrate. Do not turn cows out in freezing weather until diluted Iodine Pro Concentrate is completely dry.

Expanded Usage: When freshening cows, begin dipping teats twice daily for about 10 days before calving.

PRECAUTION: Iodine Pro Concentrate is not intended to cure or help the healing of chapped or irritated teats. As with any germicide, irritation or sensitization may occur in sensitive animals. In case of teat irritation or chapping, have the condition examined and, if necessary, treated by a veterinarian.

NOTE: Use blended Iodine Pro Concentrate within six (6) months of blended date.

Principal display panel and representative container

ASPEN IODINE PRO CONCENTRATE

ACTIVE INGREDIENT:

Titratable iodine...................................................................................4.0%

INERT INGREDIENTS:............................................................................ 96.0%

(contains glycerin, propylene glycol)

TOTAL:................................................................................................100.0%

Iodine Teat Dip Concentrate

An aid in reducing the spread of organisms which may cause mastitis

208 L (55 US GAL)

6302354

Manufactured for:

Aspen Veterinary Resources®, Ltd. 3155 Heartland Drive, Liberty, MO 64068 1-800-203-5620

778199/5300/1021